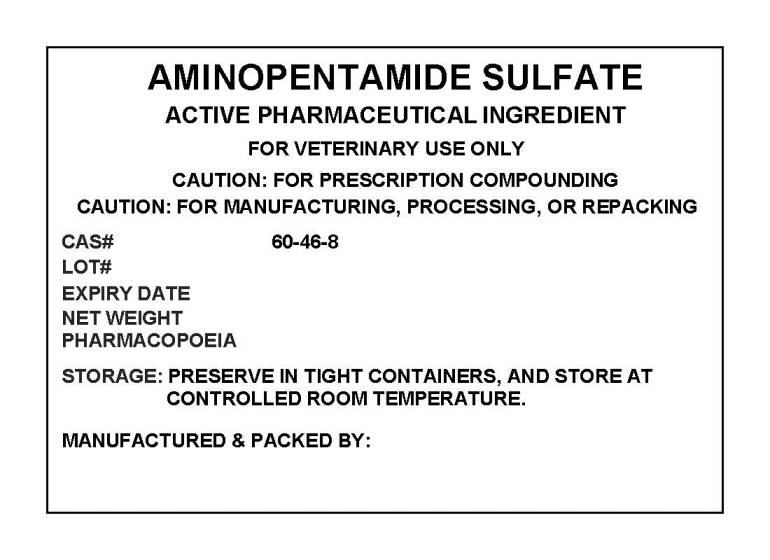 DRUG LABEL: AMINOPENTAMIDE SULFATE
NDC: 72969-002 | Form: POWDER
Manufacturer: PROFESSIONAL GROUP OF PHARMACISTS NEW YORK LLC
Category: other | Type: BULK INGREDIENT
Date: 20220101

ACTIVE INGREDIENTS: AMINOPENTAMIDE SULFATE 1 g/1 g

AMINOPENTAMIDE SULFATE

PACKAGE LABEL

aminopentamidelabel.jpg